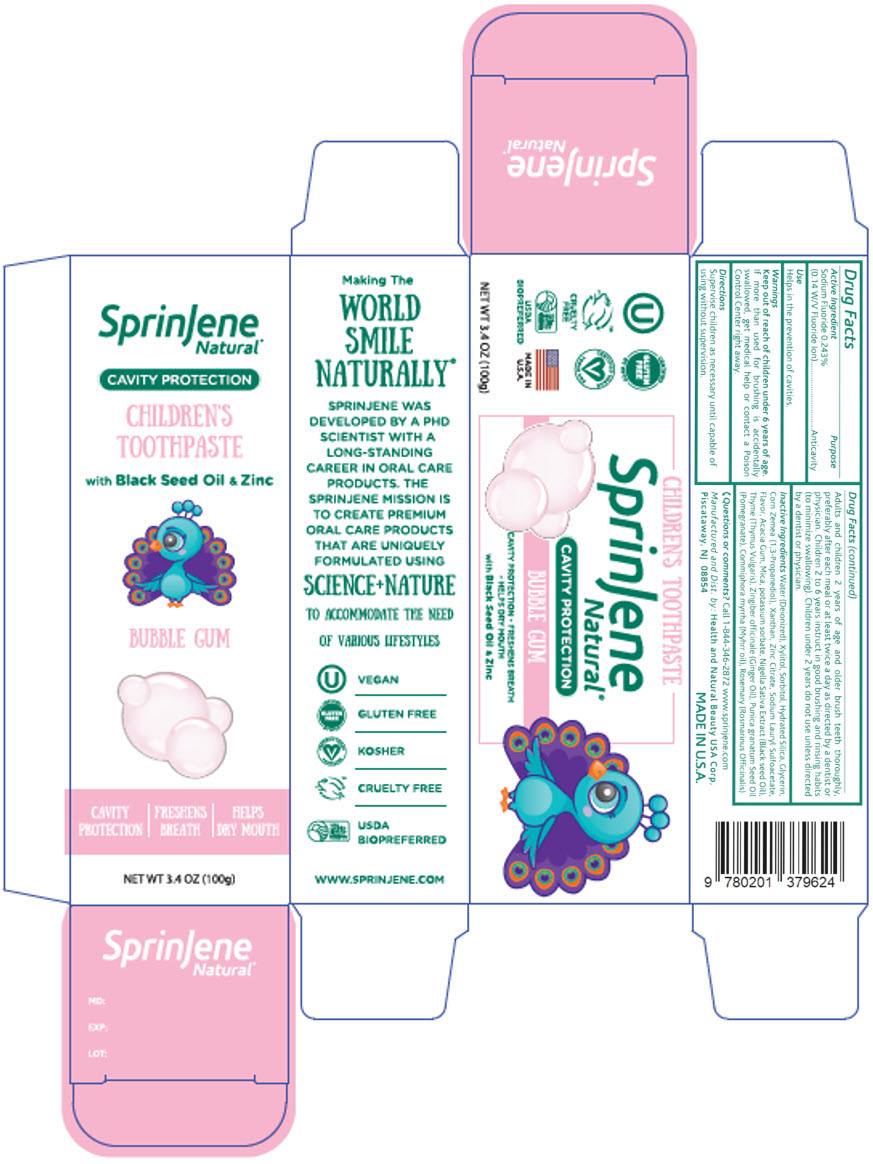 DRUG LABEL: SprinJene 
NDC: 63404-0229 | Form: PASTE, DENTIFRICE
Manufacturer: Health and Natural Beauty USA Corp
Category: otc | Type: HUMAN OTC DRUG LABEL
Date: 20240507

ACTIVE INGREDIENTS: Sodium Fluoride 1.5 mg/1 g
INACTIVE INGREDIENTS: WATER; Xylitol; Sorbitol; Hydrated Silica; Glycerin; PROPANEDIOL; Xanthan Gum; Zinc Citrate; Sodium Lauryl Sulfoacetate; ACACIA; Mica; Potassium Sorbate; NIGELLA SATIVA SEED OIL; Thyme; GINGER OIL; POMEGRANATE SEED OIL; MYRRH OIL; ROSEMARY

SprinJene
Natural® Bubble Gum

Drug Facts

Active Ingredient

Sodium Fluoride 0.243 % (0.14 W/V Fluoride Ion)

Purpose

Anticavity

Use

Helps in the prevention of cavities.

Warnings

Keep out of reach of children under 6 years of age.

If more than used for brushing is accidentally swallowed, get medical help or contact a Poison Control Center right away.

Directions

Supervise children as necessary until capable of using without supervision.

Adults and children 2 years of age and older brush teeth thoroughly, preferably after each meal or at least twice a day as directed by a dentist or physician. Children 2 to 6 years instruct in good brushing and rinsing habits (to minimize swallowing). Children under 2 years do not use unless directed by a dentist or physician.

Inactive Ingredients

Water (Deionized), Xylitol, Sorbitol, Hydrated Silica, Glycerin, Corn Zemea (1,3-Propanediol), Xanthan, Zinc Citrate, Sodium Lauryl Sulfoacetate, Flavor, Acacia Gum, Mica, potassium sorbate, Nigella Sativa Extract (Black seed Oil), Thyme (Thymus Vulgaris), Zingiber officinale (Ginger Oil), Punica granatum Seed Oil (Pomegranate), Commiphora myrrha (Myhrr oil), Rosemary (Rosmarinus Officinalis)

Questions or comments?

Call 1-844-346-2872

www.sprinjene.com

Manufactured and Dist. by: Health and Natural Beauty USA Corp,
Piscataway, NJ 08854

PRINCIPAL DISPLAY PANEL - 100 g Tube Carton

SprinJene
Natural®

CAVITY PROTECTION

CHILDREN'S
TOOTHPASTE

with Black Seed Oil & Zinc

BUBBLE GUM

CAVITY
PROTECTION

FRESHENS
BREATH

HELPS
DRY MOUTH

NET WT 3.4 OZ (100g)